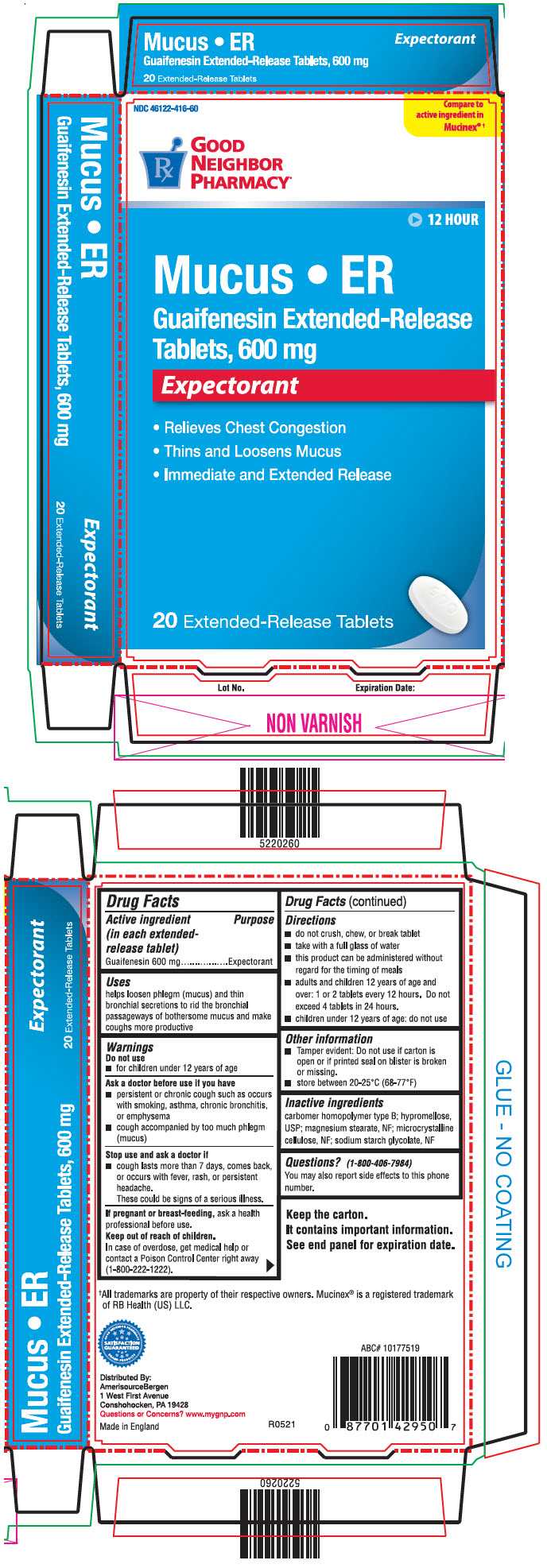 DRUG LABEL: Mucus
NDC: 46122-416 | Form: TABLET, EXTENDED RELEASE
Manufacturer: AMERISOURCEBERGEN DRUG CORPORATION
Category: otc | Type: HUMAN OTC DRUG LABEL
Date: 20210603

ACTIVE INGREDIENTS: Guaifenesin 600 mg/1 1
INACTIVE INGREDIENTS: CARBOMER HOMOPOLYMER TYPE B (ALLYL PENTAERYTHRITOL CROSSLINKED); HYPROMELLOSE, UNSPECIFIED; MAGNESIUM STEARATE; MICROCRYSTALLINE CELLULOSE; SODIUM STARCH GLYCOLATE TYPE A POTATO

Mucus
Extended Release

Drug Facts

Active ingredient (in each extended-release tablet)

Guaifenesin 600 mg

Purpose

Expectorant

Uses

helps loosen phlegm (mucus) and thin bronchial secretions to rid the bronchial passageways of bothersome mucus and make coughs more productive

Warnings

Do not use

- for children under 12 years of age

Ask a doctor before use if you have

- persistent or chronic cough such as occurs with smoking, asthma, chronic bronchitis, or emphysema
- cough accompanied by too much phlegm (mucus)

Stop use and ask a doctor if

- cough lasts more than 7 days, comes back, or occurs with fever, rash, or persistent headache.
  These could be signs of a serious illness.

PREGNANCY OR BREAST FEEDING

If pregnant or breast-feeding, ask a health professional before use.

Keep out of reach of children.

In case of overdose, get medical help or contact a Poison Control Center right away (1-800-222-1222).

Directions

- do not crush, chew, or break tablet
- take with a full glass of water
- this product can be administered without regard for the timing of meals
- adults and children 12 years of age and over: 1 or 2 tablets every 12 hours. Do not exceed 4 tablets in 24 hours.
- children under 12 years of age: do not use

Other information

- Tamper evident: Do not use if carton is open or if printed seal on blister is broken or missing.
- store between 20-25°C (68-77°F)

Inactive ingredients

carbomer homopolymer type B; hypromellose, USP; magnesium stearate, NF; microcrystalline cellulose, NF; sodium starch glycolate, NF

Questions?

(1-800-406-7984)

You may also report side effects to this phone number.

Distributed By:
AmerisourceBergen,
1300 Morris Drive
Chesterbrook, PA 19087

PRINCIPAL DISPLAY PANEL - 600 mg Tablet Blister Pack Carton

NDC 46122-416-60

Compare to
active ingredient in
Mucinex® †

GOOD
NEIGHBOR
PHARMACY®

12 HOUR

Mucus • ER
Guaifenesin Extended-Release
Tablets, 600 mg

Expectorant

- Relieves Chest Congestion
- Thins and Loosens Mucus
- Immediate and Extended Release

20 Extended-Release Tablets